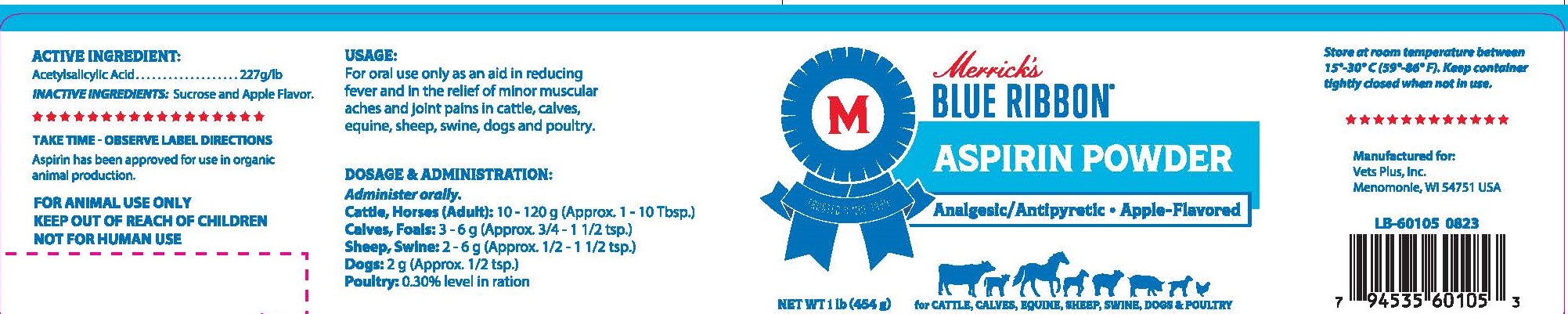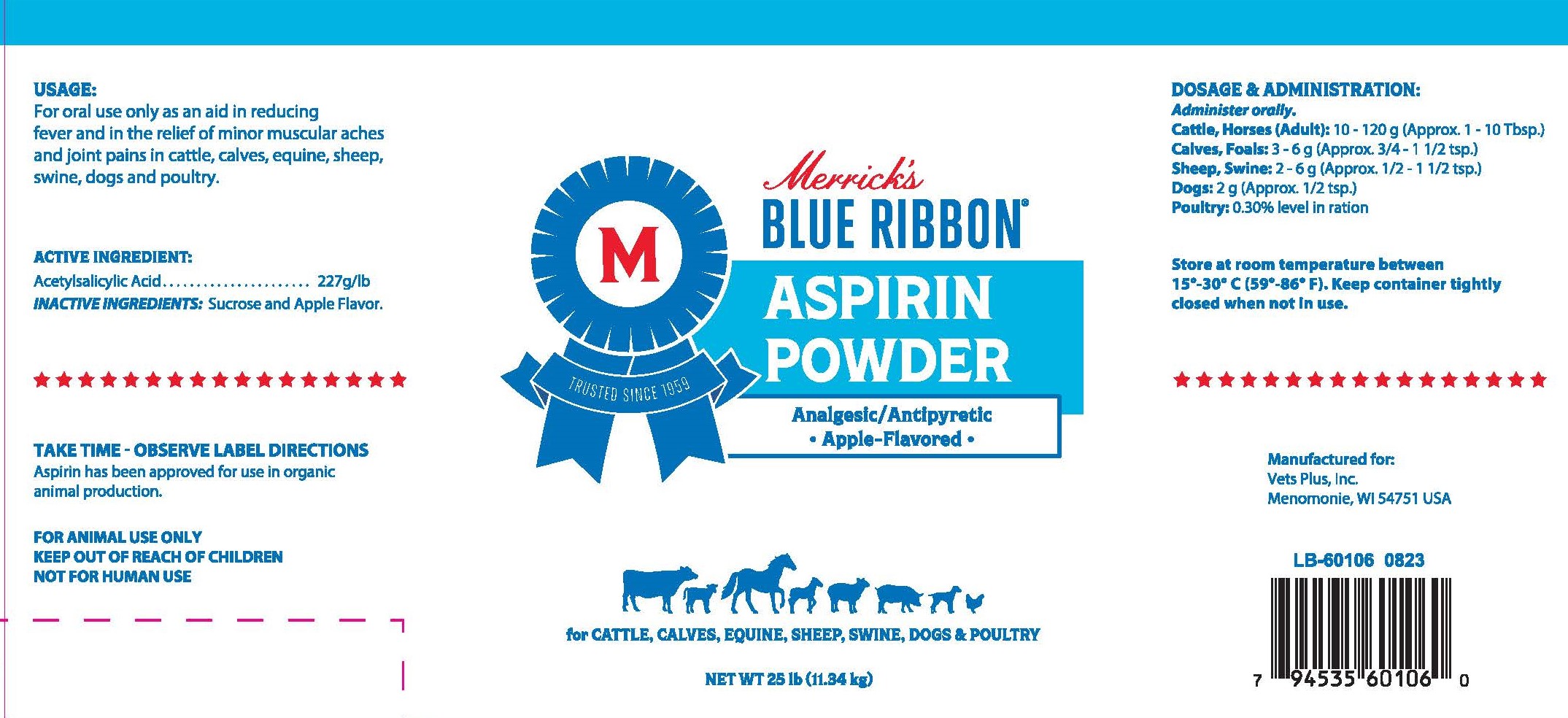 DRUG LABEL: MBR Aspirin Powder
NDC: 86118-601 | Form: POWDER
Manufacturer: Merrick's Animal Health, LLC.
Category: animal | Type: OTC ANIMAL DRUG LABEL
Date: 20250129

ACTIVE INGREDIENTS: ASPIRIN 500 mg/1 g

Usage:

For oral use only as an aid in reducing fever and in the relief of minor muscular aches and joint pains in cattle, calves, equine, sheep, swine, dogs and poultry.

Dosage and Administration:

Administer Orally

Cattle, Horses (Adult): 10-120g (approx. 1-10 Tbsp.)

Calves, Foals: 3-6g (approx. 3/4-1 1/2 tsp.)

Sheep, Swine: 2-6g (approx. 1/2-1 1/2 tsp.)

Dogs: 2g (approx. 1/2 tsp.)

Poultry: 0.30% level in ration

Active Ingredients:

Acetylsalicylic Acid.............227g/lb

Inactive Ingredients:

Sucrose and Apple Flavor

Label- One Pound Container

Label- 25 Pound Container